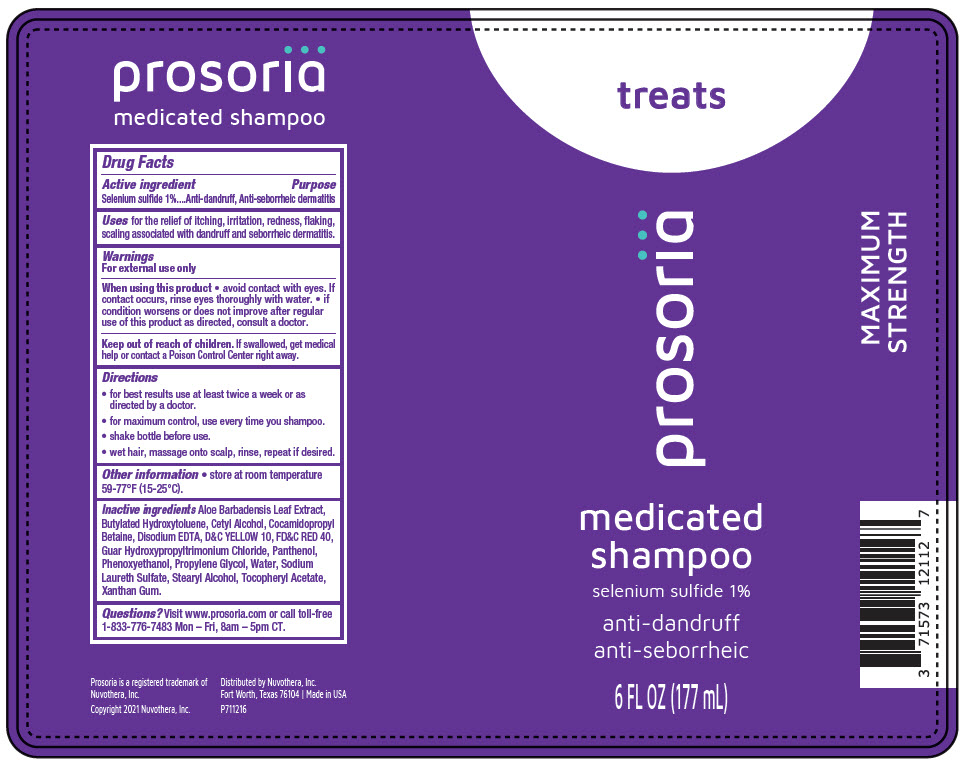 DRUG LABEL: Prosoria Medicated
NDC: 71573-121 | Form: LOTION/SHAMPOO
Manufacturer: Nuvothera, Inc.
Category: otc | Type: HUMAN OTC DRUG LABEL
Date: 20240111

ACTIVE INGREDIENTS: Selenium Sulfide 1.77 g/177 mL
INACTIVE INGREDIENTS: Water; Cetyl alcohol; GUAR HYDROXYPROPYLTRIMONIUM CHLORIDE (1.7 SUBSTITUENTS PER SACCHARIDE); Aloe Vera Leaf; Butylated Hydroxytoluene; Cocamidopropyl Betaine; D&C Yellow No. 10; Edetate Disodium Anhydrous; FD&C Red No. 40; Panthenol; Propylene Glycol; Stearyl Alcohol; .ALPHA.-TOCOPHEROL ACETATE; Xanthan Gum; Sodium Laureth-3 Sulfate; Phenoxyethanol

Prosoria Medicated Shampoo

Drug Facts

Active ingredient

Selenium sulfide 1%

Purpose

Anti-dandruff, Anti-seborrheic dermatitis

Uses

for the relief of itching, irritation, redness, flaking, scaling associated with dandruff and seborrheic dermatitis.

Warnings

For external use only

When using this product

- avoid contact with eyes. If contact occurs, rinse eyes thoroughly with water.
- if condition worsens or does not improve after regular use of this product as directed, consult a doctor.

Keep out of reach of children. If swallowed, get medical help or contact a Poison Control Center right away.

Directions

- for best results use at least twice a week or as directed by a doctor.
- for maximum control, use every time you shampoo.
- shake bottle before use.
- wet hair, massage onto scalp, rinse, repeat if desired.

Other information

- store at room temperature 59-77°F (15-25°C).

Inactive ingredients

Aloe Barbadensis Leaf Extract, Butylated Hydroxytoluene, Cetyl Alcohol, Cocamidopropyl Betaine, Disodium EDTA, D&C YELLOW 10, FD&C RED 40, Guar Hydroxypropyltrimonium Chloride, Panthenol, Phenoxyethanol, Propylene Glycol, Water, Sodium Laureth Sulfate, Stearyl Alcohol, Tocopheryl Acetate, Xanthan Gum.

Questions?

Visit www.prosoria.com or call toll-free 1-833-776-7483 Mon – Fri, 8am – 5pm CT.

Distributed by Nuvothera, Inc.
Fort Worth, Texas 76104

PRINCIPAL DISPLAY PANEL - 177 mL Bottle Label

treats

prosoriä

medicated
shampoo

selenium sulfide 1%

anti-dandruff
anti-seborrheic

6 FL OZ (177 mL)